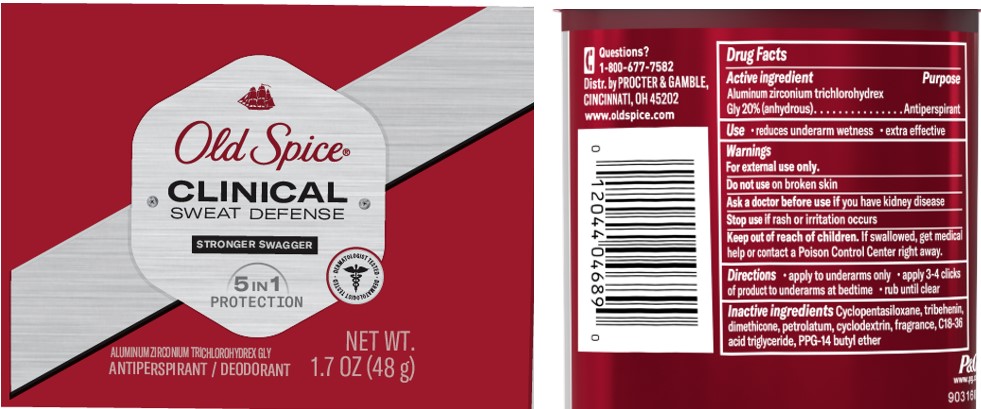 DRUG LABEL: Old Spice Clinical Sweat Defense Stronger Swagger Soft
NDC: 69423-518 | Form: STICK
Manufacturer: The Procter & Gamble Manufacturing Company
Category: otc | Type: HUMAN OTC DRUG LABEL
Date: 20250827

ACTIVE INGREDIENTS: ALUMINUM ZIRCONIUM TRICHLOROHYDREX GLY 20 g/100 g
INACTIVE INGREDIENTS: CYCLOPENTASILOXANE; DIMETHICONE; PETROLATUM; TRIBEHENIN; PPG-14 BUTYL ETHER; C18-36 ACID TRIGLYCERIDE; CYCLODEXTRINS

Old Spice® Clinical Sweat Defense Stronger Swagger Soft Solid

Drug Facts

Active ingredient

Aluminum zirconium trichlorohydrex Gly 20% (anhydrous)

Purpose

Antiperspirant

Use

reduces underarm wetness

Warnings

For external use only.

Do not use on broken skin

Ask a doctor before use if you have kidney disease

Stop use if rash or irritation occurs

Keep out of reach of children.

If swallowed, get medical help or contact a Poison Control Center right away.

Directions

- apply to underarms only
- apply 3-4 clicks of product to underarms at bedtime
- rub until clear

Inactive ingredients

Cyclopentasiloxane, tribehenin, dimethicone, petrolatum, cyclodextrin, fragrance, C18-36 acid triglyceride, PPG-14 butyl ether

Questions?

1-800-677-7582

Dist. by PROCTER & GAMBLE,
CINCINNATI, OH 45202.

PRINCIPAL DISPLAY PANEL - 48 g CYLINDER

Old Spice®

CLINICAL

SWEAT DEFENSE

STRONGER SWAGGER

ALUMINUM ZIRCONIUM TRICHLOROHYDREX GLY

ANTIPERSPIRANT/DEODORANT

NET WT. 1.7 OZ (48 g)